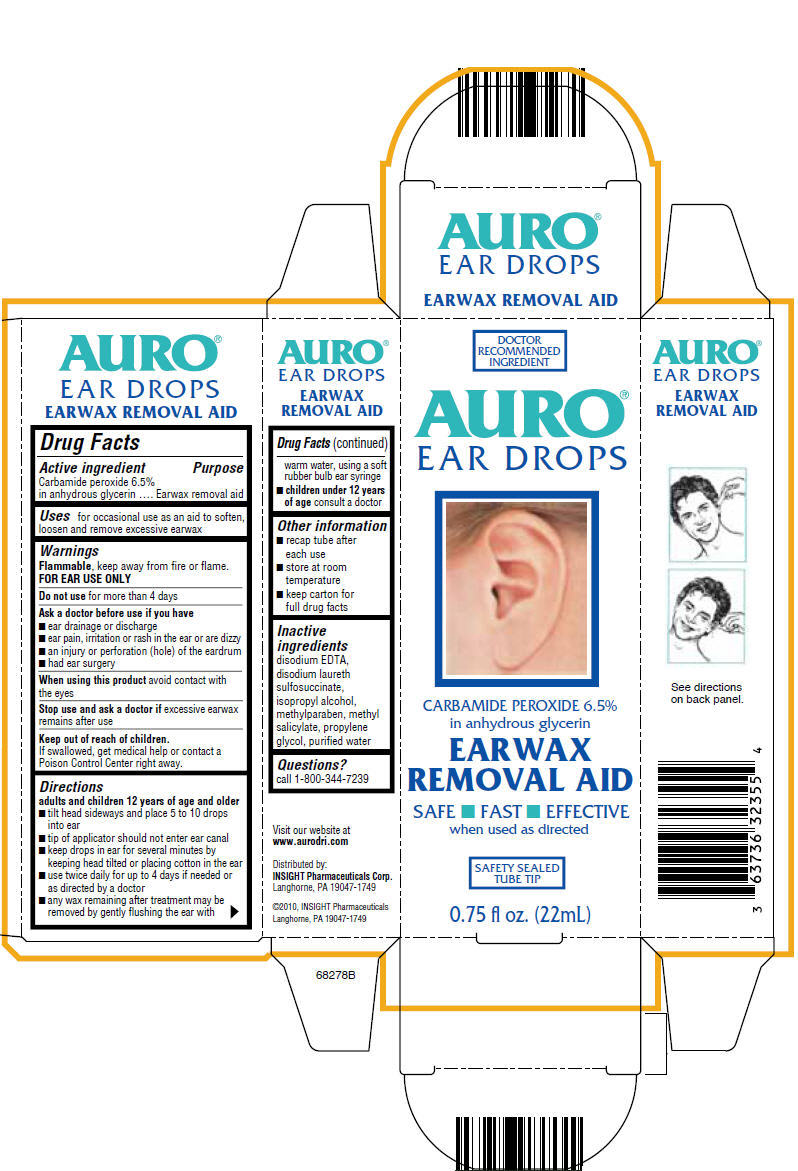 DRUG LABEL: Auro Ear Wax Remover
NDC: 63736-232 | Form: LIQUID
Manufacturer: Insight Pharmaceuticals LLC
Category: otc | Type: HUMAN OTC DRUG LABEL
Date: 20110131

ACTIVE INGREDIENTS: Carbamide peroxide 1.44 mL/22 mL
INACTIVE INGREDIENTS: Edetate Disodium; Disodium Laureth Sulfosuccinate; Isopropyl Alcohol; Methylparaben; Methyl Salicylate; Propylene Glycol; Water

AURO®
EAR DROPS
EARWAX REMOVAL AID

Drug Facts

Active ingredient

Carbamide peroxide 6.5% in anhydrous glycerin

Purpose

Earwax removal aid

Uses

for occasional use as an aid to soften, loosen and remove excessive earwax

Warnings

Flammable, keep away from fire or flame.

FOR EAR USE ONLY

Do not use for more than 4 days

Ask a doctor before use if you have

- ear drainage or discharge
- ear pain, irritation or rash in the ear or are dizzy
- an injury or perforation (hole) of the eardrum
- had ear surgery

When using this product avoid contact with the eyes

Stop use and ask a doctor if excessive earwax remains after use

Keep out of reach of children.

If swallowed, get medical help or contact a Poison Control Center right away.

Directions

adults and children 12 years of age and older

- tilt head sideways and place 5 to 10 drops into ear
- tip of applicator should not enter ear canal
- keep drops in ear for several minutes by keeping head tilted or placing cotton in the ear
- use twice daily for up to 4 days if needed or as directed by a doctor
- any wax remaining after treatment may be removed by gently flushing the ear with warm water, using a soft rubber bulb ear syringe
- children under 12 years of age consult a doctor

Other information

- recap tube after each use
- store at room temperature
- keep carton for full drug facts

Inactive ingredients

disodium EDTA, disodium laureth sulfosuccinate, isopropyl alcohol, methylparaben, methyl salicylate, propylene glycol, purified water

Questions?

call 1-800-344-7239

Distributed:
INSIGHT Pharmaceuticals Corp.
Langhorne, PA 19047-1749

PRINCIPAL DISPLAY PANEL - 22mL Tube Carton

DOCTOR
RECOMMENDED
INGREDIENT

AURO®
EAR DROPS

CARBAMIDE PEROXIDE 6.5%
in anhydrous glycerin

EARWAX
REMOVAL AID

SAFE ■ FAST ■ EFFECTIVE
when used as directed

SAFETY SEALED
TUBE TIP

0.75 fl oz. (22mL)